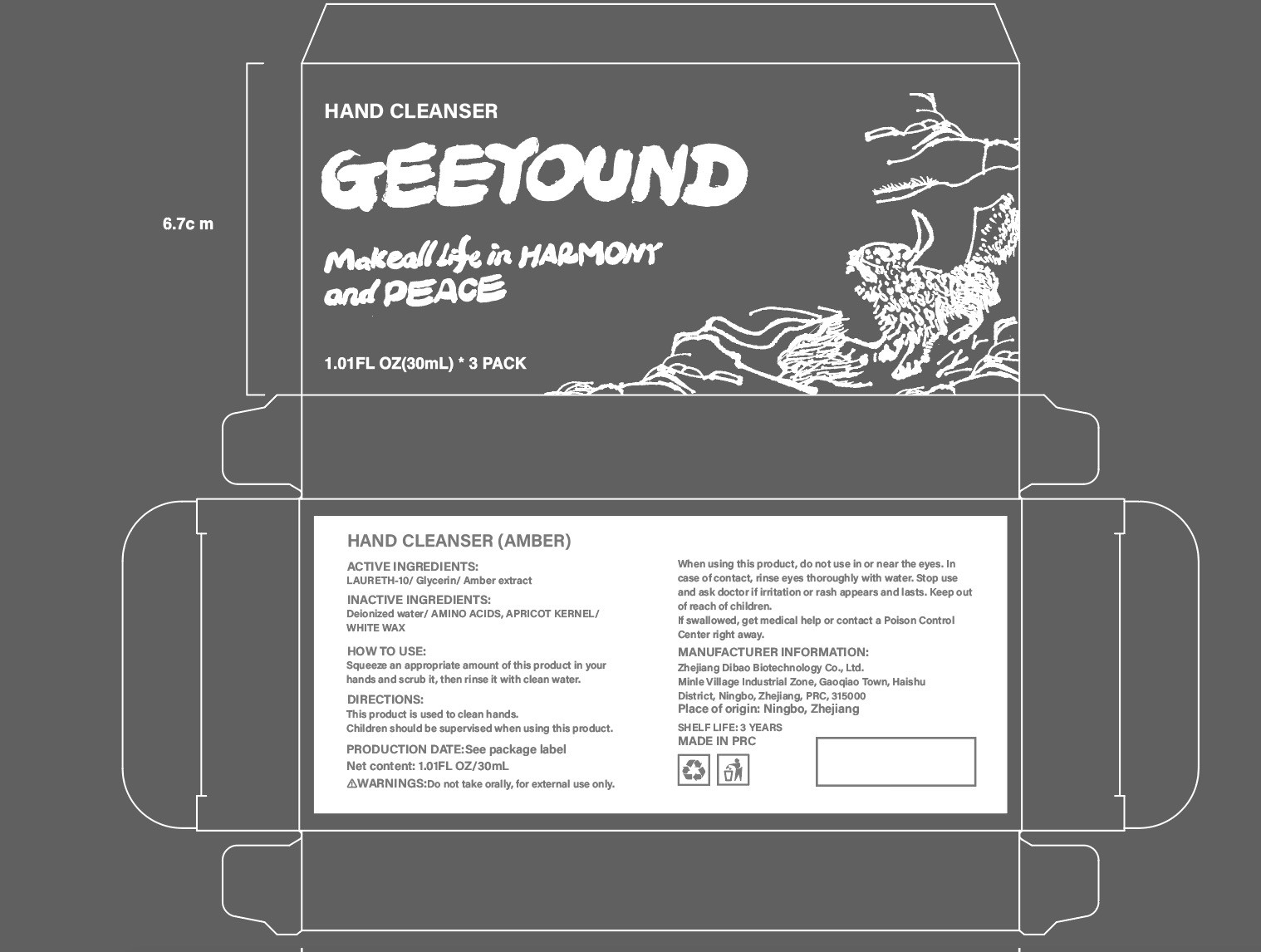 DRUG LABEL: Hand cleanser
NDC: 82371-008 | Form: LIQUID
Manufacturer: Zhejiang Dibao Biotechnology Co., Ltd.
Category: otc | Type: HUMAN OTC DRUG LABEL
Date: 20211228

ACTIVE INGREDIENTS: AMBER 10.2 g/100 mL; LAURETH-10 6 g/100 mL; GLYCERIN 3 g/100 mL
INACTIVE INGREDIENTS: WATER; WHITE WAX; AMINO ACIDS, APRICOT KERNEL

ACTIVE INGREDIENT

LAURETH-10 6%

Glycerin 3%

Amber extract 10.2%

INACTIVE INGREDIENT

Deionized water

AMINO ACIDS, APRICOT KERNEL

WHITE WAX

HOW TO USE

Squeeze an appropriate amount of this product in your hands and scrub it, then rinse it with clean water.

DIRECTIONS

This product is used to clean hands.

Children should be supervised when using this product

Keep out of reach of children.

PURPOSE

clean

STORAGE AND HANDLING

Keep in a cool and dry place

WARNINGS

Do not take orally, for external use only.

When using this product, do not use in or near the eyes. In case of contact, rinse eyes thoroughly with water. Stop use and ask doctor if irritation or rash appears and lasts.Keep out of reach of children.
lf swallowed, get medical help or contact a Poison Control Center right away.